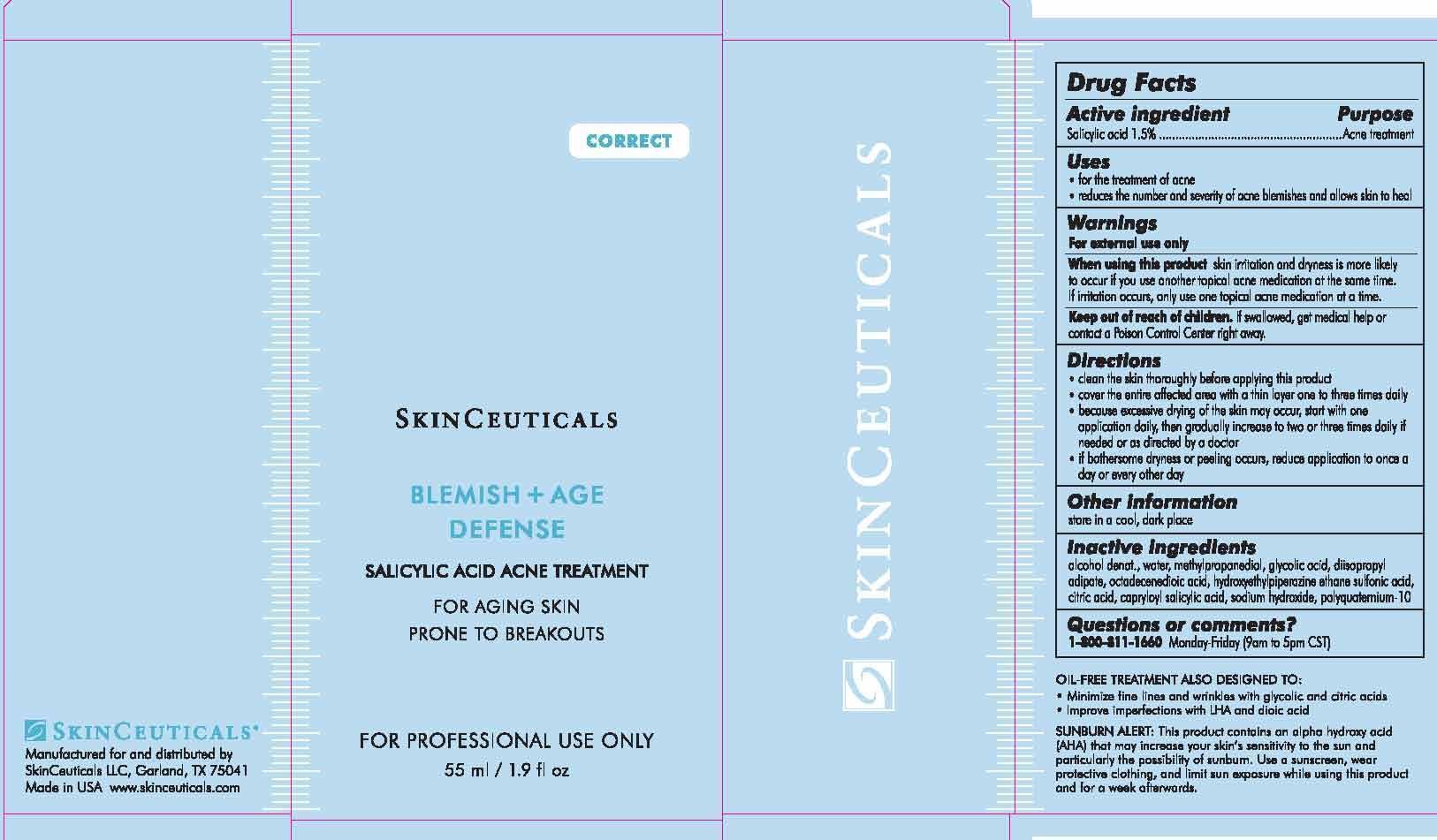 DRUG LABEL: SkinCeuticals Blemish Plus Age Defense Acne Treatment
NDC: 49967-097 | Form: LOTION
Manufacturer: L'Oreal USA Products Inc
Category: otc | Type: HUMAN OTC DRUG LABEL
Date: 20241227

ACTIVE INGREDIENTS: SALICYLIC ACID 15 mg/1 mL
INACTIVE INGREDIENTS: ALCOHOL; WATER; METHYLPROPANEDIOL; GLYCOLIC ACID; DIISOPROPYL ADIPATE; OCTADECENEDIOIC ACID; HYDROXYETHYLPIPERAZINE ETHANE SULFONIC ACID; CITRIC ACID MONOHYDRATE; CAPRYLOYL SALICYLIC ACID; SODIUM HYDROXIDE; POLYQUATERNIUM-69 (350000 MW)

Drug Facts

Active ingredient

Salicylic acid 1.5%

Purpose

Acne treatment

Uses

- for the treatment of acne

- reduces the number and severity of acne blemishes and allows skin to heal

Warnings

For external use only

When using this product

skin irritation and dryness is more liekly to occur if you use another topical acne medication at the same time. If irritation occurs, only use one topical acne medication at a time.

Keep out of reach of children.

If swallowed, get medical help or contact a Poison Control Center right away.

Directions

- clean the skin thoroughly before applying this product

- cover the entire affected area with a thin layer one to three times daily

- because excessive drying of the skin may occur, start with one application daily, then gradually increase to two or three times daily if needed or as directed by a doctor

- if bothersome dryness or peeling occurs, reduce application to once a day or every other day

Other information

store in a cool, dark place

Inactive ingredients

alcohol denat., water, methylpropanediol, glycolic acid, diisopropyl adipate, octadecenedioic acid, hydroxethylpiperazine ethane sulfonic acid, citric acid, capryloyl salicylic acid, sodium hydroxide, polyquaternium-10

Questions or comments?

1-800-811-1660

Monday - Friday (9 a.m. - 5 p.m. CST)